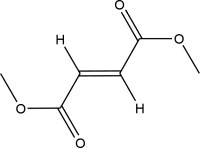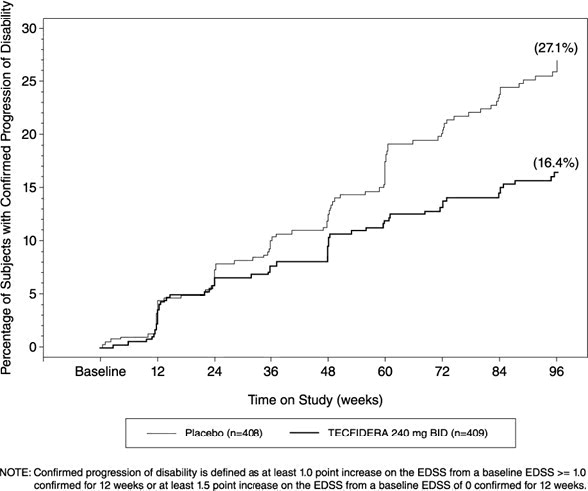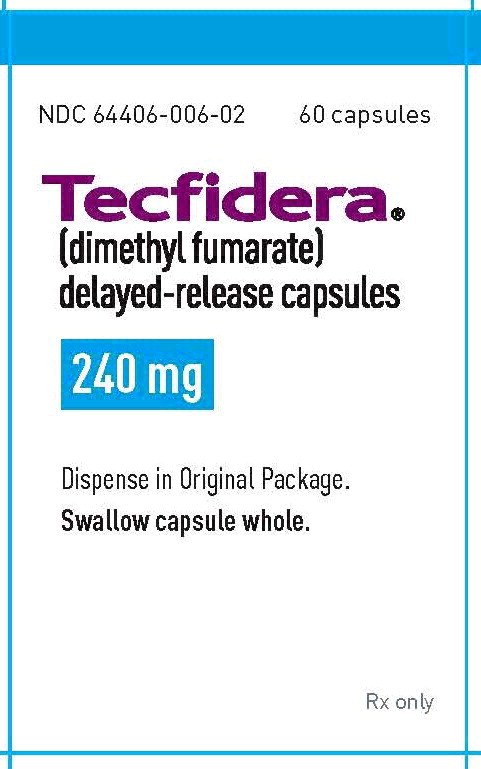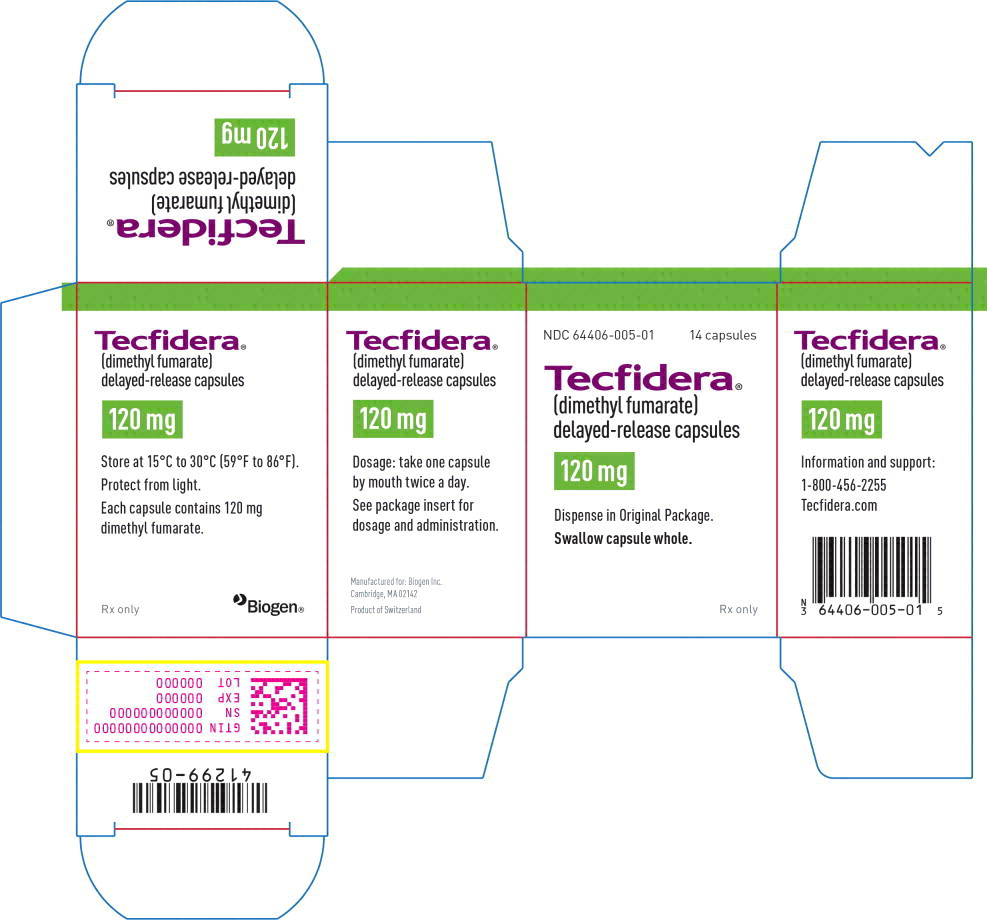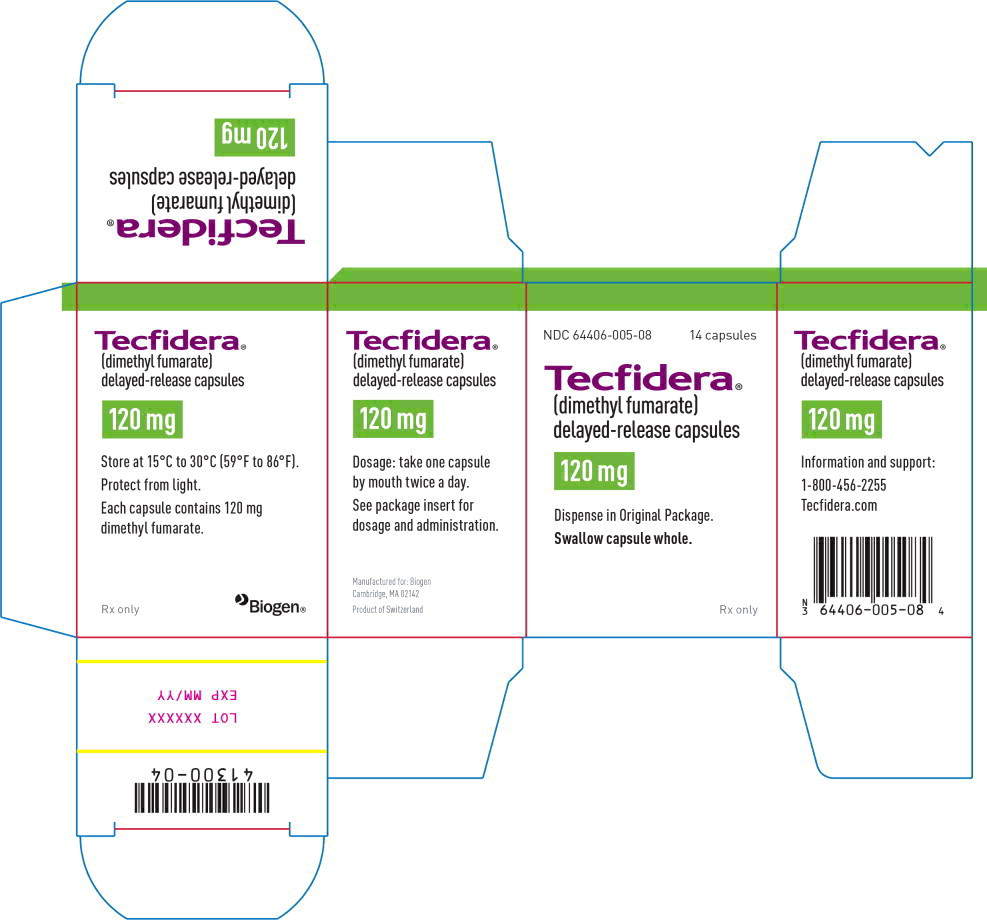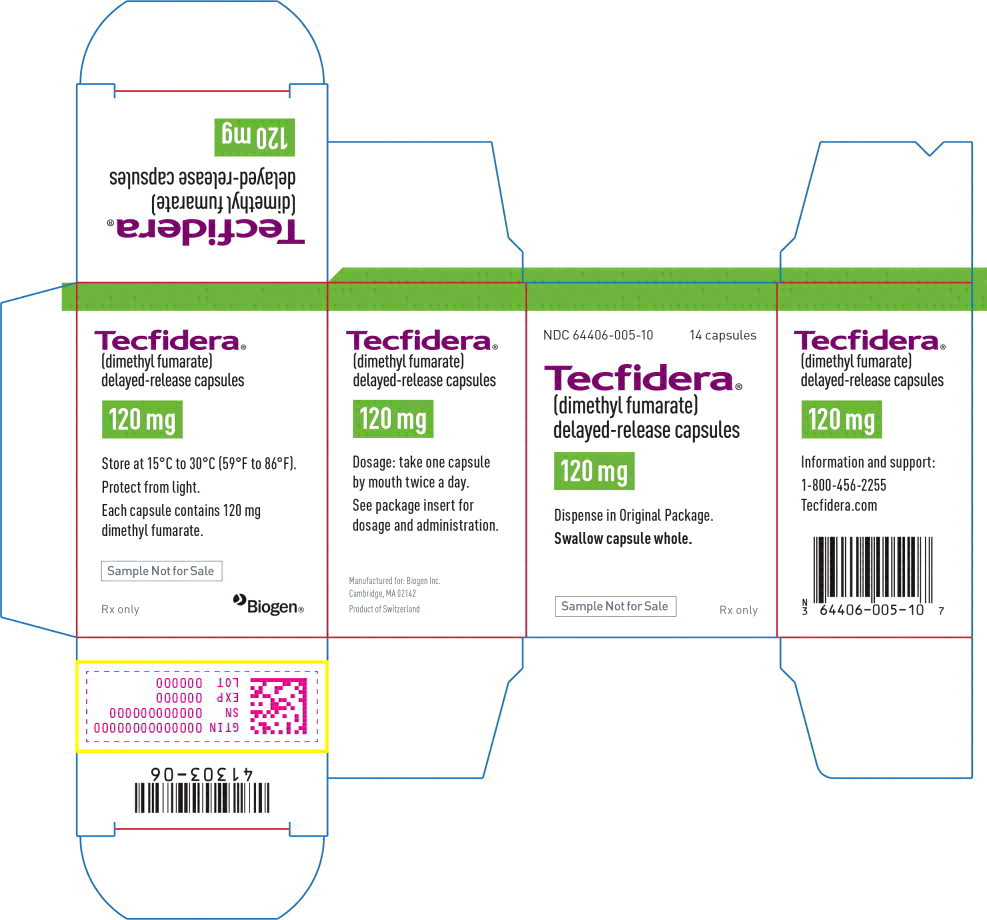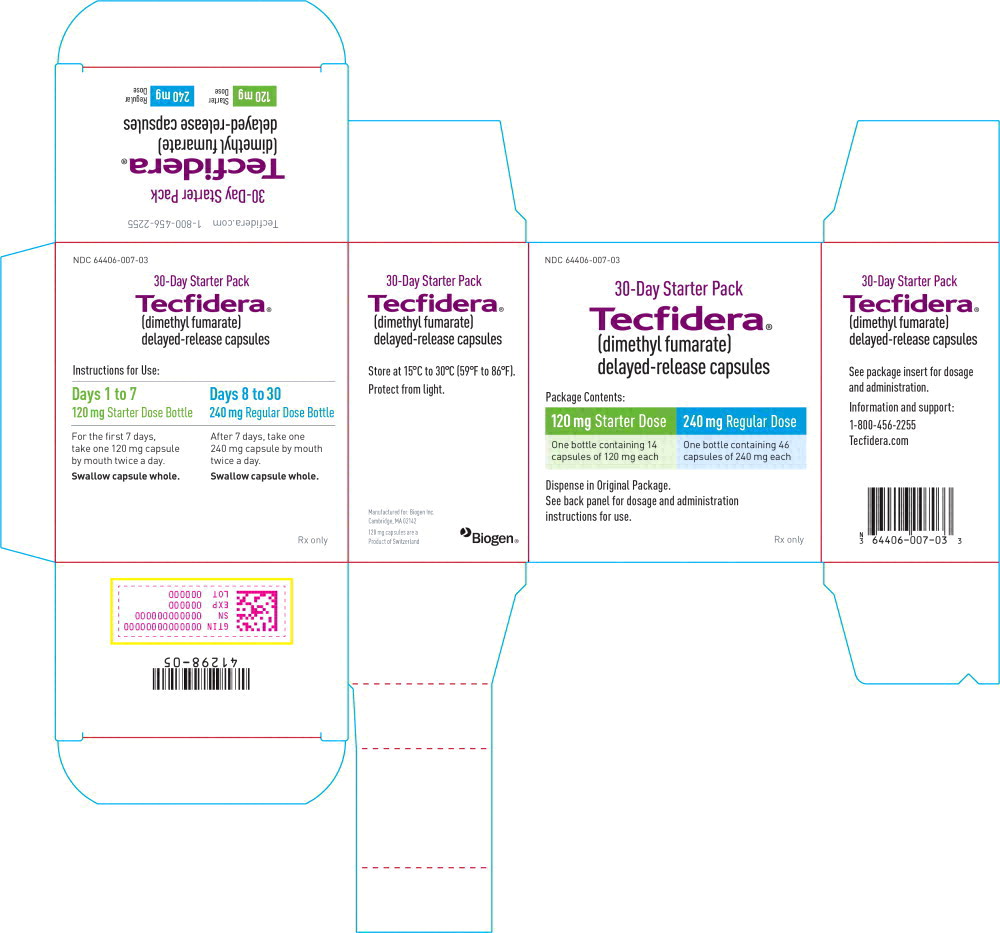 DRUG LABEL: Tecfidera
NDC: 64406-007 | Form: KIT | Route: ORAL
Manufacturer: Biogen Inc.
Category: prescription | Type: HUMAN PRESCRIPTION DRUG LABEL
Date: 20250604

ACTIVE INGREDIENTS: dimethyl fumarate 120 mg/1 1; dimethyl fumarate 240 mg/1 1
INACTIVE INGREDIENTS: Croscarmellose sodium; Microcrystalline Cellulose; Silicon dioxide; Methacrylic Acid - Methyl Methacrylate Copolymer (1:1); Triethyl citrate; Methacrylic Acid - Ethyl Acrylate Copolymer (1:1) Type A; Talc; Magnesium stearate; dimethicone; sodium lauryl sulfate; polysorbate 80; Gelatin, Unspecified; Titanium Dioxide; FD&C Blue No. 1; Ferric Oxide Yellow; FERROSOFERRIC OXIDE; Croscarmellose sodium; Microcrystalline Cellulose; Silicon dioxide; Methacrylic Acid - Methyl Methacrylate Copolymer (1:1); Triethyl citrate; Methacrylic Acid - Ethyl Acrylate Copolymer (1:1) Type A; Talc; Magnesium stearate; dimethicone; sodium lauryl sulfate; polysorbate 80; Gelatin, Unspecified; Titanium Dioxide; FD&C Blue No. 1; Ferric Oxide Yellow; FERROSOFERRIC OXIDE

HIGHLIGHTS OF PRESCRIBING INFORMATION

These highlights do not include all the information needed to use TECFIDERA safely and effectively. See full prescribing information for TECFIDERA.
TECFIDERA® (dimethyl fumarate) delayed-release capsules, for oral use
Initial U.S. Approval: 2013

RECENT MAJOR CHANGES

Warnings and Precautions, Serious Gastrointestinal Reactions (5.7) | 12/2023

1 INDICATIONS AND USAGE

TECFIDERA is indicated for the treatment of relapsing forms of multiple sclerosis (MS), to include clinically isolated syndrome, relapsing-remitting disease, and active secondary progressive disease, in adults. (1)

2 DOSAGE AND ADMINISTRATION

- Starting dose: 120 mg twice a day, orally, for 7 days (2.1)
- Maintenance dose after 7 days: 240 mg twice a day, orally (2.1)
- Swallow TECFIDERA capsules whole and intact. Do not crush, chew, or sprinkle capsule contents on food (2.1)
- Take TECFIDERA with or without food (2.1)

3 DOSAGE FORMS AND STRENGTHS

Delayed-release capsules: 120 mg and 240 mg (3)

4 CONTRAINDICATIONS

Known hypersensitivity to dimethyl fumarate or any of the excipients of TECFIDERA. (4)

5 WARNINGS AND PRECAUTIONS

- Anaphylaxis and Angioedema: Discontinue and do not restart TECFIDERA if these occur. (5.1)
- Progressive Multifocal Leukoencephalopathy (PML): Withhold TECFIDERA at the first sign or symptom suggestive of PML. (5.2)
- Herpes Zoster and Other Serious Opportunistic Infections: Consider withholding TECFIDERA in cases of serious infection until the infection has resolved. (5.3)
- Lymphopenia: Obtain a CBC including lymphocyte count before initiating TECFIDERA, after 6 months, and every 6 to 12 months thereafter. Consider interruption of TECFIDERA if lymphocyte counts <0.5 x 10^9/L persist for more than six months. (5.4)
- Liver Injury: Obtain serum aminotransferase, alkaline phosphatase, and total bilirubin levels before initiating TECFIDERA and during treatment, as clinically indicated. Discontinue TECFIDERA if clinically significant liver injury induced by TECFIDERA is suspected. (5.5)

6 ADVERSE REACTIONS

Most common adverse reactions (incidence ≥10% and ≥2% placebo) were flushing, abdominal pain, diarrhea, and nausea. (6.1)

To report SUSPECTED ADVERSE REACTIONS, contact Biogen at 1-800-456-2255 or FDA at 1-800-FDA-1088 or www.fda.gov/medwatch.

FULL PRESCRIBING INFORMATION

1 INDICATIONS AND USAGE

TECFIDERA is indicated for the treatment of relapsing forms of multiple sclerosis (MS), to include clinically isolated syndrome, relapsing-remitting disease, and active secondary progressive disease, in adults.

2 DOSAGE AND ADMINISTRATION

2.1 Dosing Information

The starting dose for TECFIDERA is 120 mg twice a day orally. After 7 days, the dose should be increased to the maintenance dose of 240 mg twice a day orally. Temporary dose reductions to 120 mg twice a day may be considered for individuals who do not tolerate the maintenance dose. Within 4 weeks, the recommended dose of 240 mg twice a day should be resumed. Discontinuation of TECFIDERA should be considered for patients unable to tolerate return to the maintenance dose. The incidence of flushing may be reduced by administration of TECFIDERA with food. Alternatively, administration of non-enteric coated aspirin (up to a dose of 325 mg) 30 minutes prior to TECFIDERA dosing may reduce the incidence or severity of flushing [see Clinical Pharmacology (12.3)].

TECFIDERA should be swallowed whole and intact. TECFIDERA should not be crushed or chewed, and the capsule contents should not be sprinkled on food. TECFIDERA can be taken with or without food.

2.2 Blood Tests Prior to Initiation of Therapy

Obtain a complete blood cell count (CBC) including lymphocyte count before initiation of therapy [see Warnings and Precautions (5.4)].

Obtain serum aminotransferase, alkaline phosphatase, and total bilirubin levels prior to treatment with TECFIDERA [see Warnings and Precautions (5.5)].

3 DOSAGE FORMS AND STRENGTHS

TECFIDERA is available as hard gelatin delayed-release capsules containing 120 mg or 240 mg of dimethyl fumarate. The 120 mg capsules have a green cap and white body, printed with “BG-12 120 mg” in black ink on the body. The 240 mg capsules have a green cap and a green body, printed with “BG-12 240 mg” in black ink on the body.

4 CONTRAINDICATIONS

TECFIDERA is contraindicated in patients with known hypersensitivity to dimethyl fumarate or to any of the excipients of TECFIDERA. Reactions have included anaphylaxis and angioedema [see Warnings and Precautions (5.1)].

5 WARNINGS AND PRECAUTIONS

5.1 Anaphylaxis and Angioedema

TECFIDERA can cause anaphylaxis and angioedema after the first dose or at any time during treatment. Signs and symptoms have included difficulty breathing, urticaria, and swelling of the throat and tongue. Patients should be instructed to discontinue TECFIDERA and seek immediate medical care should they experience signs and symptoms of anaphylaxis or angioedema.

5.2 Progressive Multifocal Leukoencephalopathy

Progressive multifocal leukoencephalopathy (PML) has occurred in patients with MS treated with TECFIDERA. PML is an opportunistic viral infection of the brain caused by the JC virus (JCV) that typically only occurs in patients who are immunocompromised, and that usually leads to death or severe disability. A fatal case of PML occurred in a patient who received TECFIDERA for 4 years while enrolled in a clinical trial. During the clinical trial, the patient experienced prolonged lymphopenia (lymphocyte counts predominantly <0.5x10^9/L for 3.5 years) while taking TECFIDERA [see Warnings and Precautions (5.4)]. The patient had no other identified systemic medical conditions resulting in compromised immune system function and had not previously been treated with natalizumab, which has a known association with PML. The patient was also not taking any immunosuppressive or immunomodulatory medications concomitantly.

PML has also occurred in the postmarketing setting in the presence of lymphopenia (<0.9x10^9/L). While the role of lymphopenia in these cases is uncertain, the PML cases have occurred predominantly in patients with lymphocyte counts <0.8x10^9/L persisting for more than 6 months.

At the first sign or symptom suggestive of PML, withhold TECFIDERA and perform an appropriate diagnostic evaluation. Typical symptoms associated with PML are diverse, progress over days to weeks, and include progressive weakness on one side of the body or clumsiness of limbs, disturbance of vision, and changes in thinking, memory, and orientation leading to confusion and personality changes.

MRI findings may be apparent before clinical signs or symptoms. Cases of PML, diagnosed based on MRI findings and the detection of JCV DNA in the cerebrospinal fluid in the absence of clinical signs or symptoms specific to PML, have been reported in patients treated with other MS medications associated with PML. Many of these patients subsequently became symptomatic with PML. Therefore, monitoring with MRI for signs that may be consistent with PML may be useful, and any suspicious findings should lead to further investigation to allow for an early diagnosis of PML, if present. Lower PML-related mortality and morbidity have been reported following discontinuation of another MS medication associated with PML in patients with PML who were initially asymptomatic compared to patients with PML who had characteristic clinical signs and symptoms at diagnosis. It is not known whether these differences are due to early detection and discontinuation of MS treatment or due to differences in disease in these patients.

5.3 Herpes Zoster and Other Serious Opportunistic Infections

Serious cases of herpes zoster have occurred with TECFIDERA, including disseminated herpes zoster, herpes zoster ophthalmicus, herpes zoster meningoencephalitis, and herpes zoster meningomyelitis. These events may occur at any time during treatment. Monitor patients on TECFIDERA for signs and symptoms of herpes zoster. If herpes zoster occurs, appropriate treatment for herpes zoster should be administered.

Other serious opportunistic infections have occurred with TECFIDERA, including cases of serious viral (herpes simplex virus, West Nile virus, cytomegalovirus), fungal (Candida and Aspergillus), and bacterial (Nocardia, Listeria monocytogenes, Mycobacterium tuberculosis) infections. These infections have been reported in patients with reduced absolute lymphocyte counts (ALC) as well as in patients with normal ALC. These infections have affected the brain, meninges, spinal cord, gastrointestinal tract, lungs, skin, eye, and ear. Patients with symptoms and signs consistent with any of these infections should undergo prompt diagnostic evaluation and receive appropriate treatment.

Consider withholding TECFIDERA treatment in patients with herpes zoster or other serious infections until the infection has resolved [see Adverse Reactions (6.2)].

5.4 Lymphopenia

TECFIDERA may decrease lymphocyte counts. In the MS placebo controlled trials, mean lymphocyte counts decreased by approximately 30% during the first year of treatment with TECFIDERA and then remained stable. Four weeks after stopping TECFIDERA, mean lymphocyte counts increased but did not return to baseline. Six percent (6%) of TECFIDERA patients and <1% of placebo patients experienced lymphocyte counts <0.5x10^9/L (lower limit of normal 0.91x10^9/L). The incidence of infections (60% vs 58%) and serious infections (2% vs 2%) was similar in patients treated with TECFIDERA or placebo, respectively. There was no increased incidence of serious infections observed in patients with lymphocyte counts <0.8x10^9/L or ≤0.5x10^9/L in controlled trials, although one patient in an extension study developed PML in the setting of prolonged lymphopenia (lymphocyte counts predominantly <0.5x10^9/L for 3.5 years) [see Warnings and Precautions (5.2)].

In controlled and uncontrolled clinical trials, 2% of patients experienced prolonged, severe lymphopenia, (defined as lymphocyte counts <0.5 x 10^9/L for at least six months); in this group of patients, the majority of lymphocyte counts remained <0.5x10^9/L with continued therapy. In these patients with prolonged, severe lymphopenia, the median time for lymphocyte counts to return to normal after discontinuing TECFIDERA was 96.0 weeks.

In these controlled and uncontrolled clinical studies, among patients who did not experience prolonged, severe lymphopenia during treatment, the median times for lymphocyte counts to return to normal after discontinuing TECFIDERA were as follows:

- 4.3 weeks in patients with mild lymphopenia (lymphocyte count ≥0.8x10^9/L) at discontinuation,
- 10.0 weeks in patients with moderate lymphopenia (lymphocyte count 0.5 to <0.8x10^9/L) at discontinuation, and
- 16.7 weeks in patients with severe lymphopenia (lymphocyte count <0.5x10^9/L) at discontinuation.

TECFIDERA has not been studied in patients with pre-existing low lymphocyte counts.

Obtain a CBC, including lymphocyte count, before initiating treatment with TECFIDERA, 6 months after starting treatment, and then every 6 to 12 months thereafter, and as clinically indicated. Consider interruption of TECFIDERA in patients with lymphocyte counts less than 0.5 x 10^9/L persisting for more than six months. Given the potential for delayed recovery of lymphocyte counts, continue to obtain lymphocyte counts until their recovery if TECFIDERA is discontinued or interrupted due to lymphopenia. Consider withholding treatment from patients with serious infections until resolution. Decisions about whether or not to restart TECFIDERA should be individualized based on clinical circumstances.

5.5 Liver Injury

Clinically significant cases of liver injury have been reported in patients treated with TECFIDERA in the postmarketing setting. The onset has ranged from a few days to several months after initiation of treatment with TECFIDERA. Signs and symptoms of liver injury, including elevation of serum aminotransferases to greater than 5-fold the upper limit of normal and elevation of total bilirubin to greater than 2-fold the upper limit of normal have been observed. These abnormalities resolved upon treatment discontinuation. Some cases required hospitalization. None of the reported cases resulted in liver failure, liver transplant, or death. However, the combination of new serum aminotransferase elevations with increased levels of bilirubin caused by drug-induced hepatocellular injury is an important predictor of serious liver injury that may lead to acute liver failure, liver transplant, or death in some patients.

Elevations of hepatic transaminases (most no greater than 3 times the upper limit of normal) were observed during controlled trials [see Adverse Reactions (6.1)].

Obtain serum aminotransferase, alkaline phosphatase (ALP), and total bilirubin levels prior to treatment with TECFIDERA and during treatment, as clinically indicated. Discontinue TECFIDERA if clinically significant liver injury induced by TECFIDERA is suspected.

5.6 Flushing

TECFIDERA may cause flushing (e.g., warmth, redness, itching, and/or burning sensation). In clinical trials, 40% of TECFIDERA treated patients experienced flushing. Flushing symptoms generally began soon after initiating TECFIDERA and usually improved or resolved over time. In the majority of patients who experienced flushing, it was mild or moderate in severity. Three percent (3%) of patients discontinued TECFIDERA for flushing and <1% had serious flushing symptoms that were not life-threatening but led to hospitalization. Administration of TECFIDERA with food may reduce the incidence of flushing. Alternatively, administration of non-enteric coated aspirin (up to a dose of 325 mg) 30 minutes prior to TECFIDERA dosing may reduce the incidence or severity of flushing [see Dosing and Administration (2.1) and Clinical Pharmacology (12.3)].

5.7 Serious Gastrointestinal Reactions

Serious gastrointestinal reactions, including perforation, ulceration, hemorrhage, and obstruction, some with fatal outcomes, have been reported in the postmarketing setting with the use of fumaric acid esters, including TECFIDERA, with or without concomitant aspirin use. The majority of these events have occurred within 6 months of fumaric acid ester treatment initiation. In controlled clinical trials, the incidence of serious gastrointestinal adverse events was 1% in patients treated with TECFIDERA; these events, none of which were fatal, included vomiting (0.3%) and abdominal pain (0.3%) [see Adverse Reactions (6.1)].

Monitor patients, promptly evaluate, and discontinue TECFIDERA for new or worsening severe gastrointestinal signs and symptoms.

6 ADVERSE REACTIONS

The following important adverse reactions are described elsewhere in labeling:

- Anaphylaxis and Angioedema [see Warnings and Precautions (5.1)].
- Progressive multifocal leukoencephalopathy [see Warnings and Precautions (5.2)].
- Herpes Zoster and Other Serious Opportunistic Infections [see Warnings and Precautions (5.3)].
- Lymphopenia [see Warnings and Precautions (5.4)].
- Liver Injury [see Warnings and Precautions (5.5)].
- Flushing [see Warnings and Precautions (5.6)].
- Serious Gastrointestinal Reactions [see Warnings and Precautions (5.7)]

6.1 Clinical Trials Experience

Because clinical trials are conducted under widely varying conditions, adverse reaction rates observed in clinical trials of a drug cannot be directly compared to rates in the clinical trials of another drug and may not reflect the rates observed in clinical practice.

In placebo-controlled and uncontrolled clinical studies, a total of 2513 patients have received TECFIDERA and been followed for periods up to 13 years with an overall exposure of 11,318 person-years. Approximately 1169 patients have received more than 5 years of treatment with TECFIDERA, and 426 patients have received at least 10 years of treatment with TECFIDERA.

Adverse Reactions in Placebo-Controlled Trials

In the two well-controlled studies demonstrating effectiveness, 1529 patients received TECFIDERA with an overall exposure of 2244 person-years [see Clinical Studies (14)].

The adverse reactions presented in the table below are based on safety information from 769 patients treated with TECFIDERA 240 mg twice a day and 771 placebo-treated patients.

The most common adverse reactions (incidence ≥10% and ≥2% more than placebo) for TECFIDERA were flushing, abdominal pain, diarrhea, and nausea.

Table 1: Adverse Reactions in Study 1 and 2 reported for TECFIDERA 240 mg BID at ≥ 2% higher incidence than placebo
 | TECFIDERA N=769 % | Placebo N=771 %
Flushing | 40 | 6
Abdominal pain | 18 | 10
Diarrhea | 14 | 11
Nausea | 12 | 9
Vomiting | 9 | 5
Pruritus | 8 | 4
Rash | 8 | 3
Albumin urine present | 6 | 4
Erythema | 5 | 1
Dyspepsia | 5 | 3
Aspartate aminotransferase increased | 4 | 2
Lymphopenia | 2 | <1

Gastrointestinal

TECFIDERA caused GI events (e.g., nausea, vomiting, diarrhea, abdominal pain, and dyspepsia). The incidence of GI events was higher early in the course of treatment (primarily in month 1) and usually decreased over time in patients treated with TECFIDERA compared with placebo. Four percent (4%) of patients treated with TECFIDERA and less than 1% of placebo patients discontinued due to gastrointestinal events. The incidence of serious GI events was 1% in clinical trial patients treated with TECFIDERA; these events, none of which were fatal, included vomiting (0.3%) and abdominal pain (0.3%).

Hepatic Transaminases

An increased incidence of elevations of hepatic transaminases in patients treated with TECFIDERA was seen primarily during the first six months of treatment, and most patients with elevations had levels < 3 times the upper limit of normal (ULN) during controlled trials. Elevations of alanine aminotransferase and aspartate aminotransferase to ≥ 3 times the ULN occurred in a small number of patients treated with both TECFIDERA and placebo and were balanced between groups. There were no elevations in transaminases ≥ 3 times the ULN with concomitant elevations in total bilirubin > 2 times the ULN. Discontinuations due to elevated hepatic transaminases were < 1% and were similar in patients treated with TECFIDERA or placebo.

Eosinophilia

A transient increase in mean eosinophil counts was seen during the first 2 months of therapy.

6.2 Postmarketing Experience

The following adverse reactions have been identified during post-approval use of TECFIDERA. Because these reactions are reported voluntarily from a population of uncertain size, it is not always possible to reliably estimate their frequency or establish a causal relationship to drug exposure.

Gastrointestinal Disorders: Acute Pancreatitis; Gastrointestinal perforation, ulceration, obstruction, and hemorrhage [see Warnings and Precautions (5.7)]

Hepatobiliary Disorders: Liver function abnormalities (elevations in transaminases ≥ 3 times ULN with concomitant elevations in total bilirubin > 2 times ULN) [see Warnings and Precautions (5.5)]

Infections and Infestations: Herpes zoster infection and other serious opportunistic infections [see Warnings and Precautions (5.3)]

Respiratory, Thoracic, and Mediastinal Disorders: Rhinorrhea

Skin and Subcutaneous: Alopecia

8 USE IN SPECIFIC POPULATIONS

8.1 Pregnancy

Risk Summary

Available data from the TECFIDERA Pregnancy Registry, observational studies, and pharmacovigilance with dimethyl fumarate use in pregnant women have not indicated an increased risk of major birth defects, miscarriage, or other adverse maternal or fetal outcomes. Most of the reported exposures to dimethyl fumarate occurred during the first trimester of pregnancy (see Data). In animals, adverse effects on offspring survival, growth, sexual maturation, and neurobehavioral function were observed when dimethyl fumarate (DMF) was administered during pregnancy and lactation at clinically relevant doses (see Data).

The background risk of major birth defects and miscarriage for the indicated population is unknown. All pregnancies have a background risk of birth defect, loss, or other adverse outcomes. In the U.S. general population, the estimated background risk of major birth defects and miscarriage in clinically recognized pregnancies is 2-4% and 15-20%, respectively.

Data

Human Data

In a prospective observational TECFIDERA Pregnancy Registry (2013-2022), the rate of major birth defects among 362 live births and stillbirths from women who were exposed to dimethyl fumarate during pregnancy was 3.6% (95% CI: 1.9-6.1). No specific pattern of major birth defects was identified. Important potential study limitations include exposure misclassification, no adjustment for confounders, and lack of an internal comparator cohort.

Animal Data

In rats administered DMF orally (25, 100, 250 mg/kg/day) throughout organogenesis, embryofetal toxicity (reduced fetal body weight and delayed ossification) were observed at the highest dose tested. This dose also produced evidence of maternal toxicity (reduced body weight). Plasma exposure (AUC) for monomethyl fumarate (MMF), the major circulating metabolite, at the no-effect dose is approximately three times that in humans at the recommended human dose (RHD) of 480 mg/day. In rabbits administered DMF orally (25, 75, and 150 mg/kg/day) throughout organogenesis, embryolethality and decreased maternal body weight were observed at the highest dose tested. The plasma AUC for MMF at the no-effect dose is approximately 5 times that in humans at the RHD.

Oral administration of DMF (25, 100, and 250 mg/kg/day) to rats throughout organogenesis and lactation resulted in increased lethality, persistent reductions in body weight, delayed sexual maturation (male and female pups), and reduced testicular weight at the highest dose tested. Neurobehavioral impairment was observed at all doses. A no-effect dose for developmental toxicity was not identified. The lowest dose tested was associated with plasma AUC for MMF lower than that in humans at the RHD.

8.2 Lactation

Risk Summary

There are no data on the presence of DMF or MMF in human milk. The effects on the breastfed infant and on milk production are unknown.

The developmental and health benefits of breastfeeding should be considered along with the mother's clinical need for TECFIDERA and any potential adverse effects on the breastfed infant from the drug or from the underlying maternal condition.

8.4 Pediatric Use

Safety and effectiveness in pediatric patients have not been established.

8.5 Geriatric Use

Clinical studies of TECFIDERA did not include sufficient numbers of patients aged 65 and over to determine whether they respond differently from younger patients.

10 OVERDOSE

Cases of overdose with TECFIDERA have been reported. The symptoms described in these cases were consistent with the known adverse event profile of TECFIDERA.

There are no known therapeutic interventions to enhance elimination of TECFIDERA nor is there a known antidote. In the event of overdose, initiate symptomatic supportive treatment as clinically indicated.

11 DESCRIPTION

TECFIDERA contains dimethyl fumarate which is also known by its chemical name, dimethyl (E) butenedioate, (C6H8O4). It has the following structure:

Dimethyl fumarate is a white to off-white powder that is highly soluble in water with a molecular mass of 144.13.

TECFIDERA is provided as hard gelatin delayed-release capsules for oral administration, containing 120 mg or 240 mg of dimethyl fumarate consisting of the following inactive ingredients: microcrystalline cellulose, silicified microcrystalline cellulose, croscarmellose sodium, talc, silica colloidal silicon dioxide, magnesium stearate, triethyl citrate, methacrylic acid copolymer - Type A, methacrylic acid copolymer dispersion, simethicone (30% emulsion), sodium lauryl sulphate, and polysorbate 80. The capsule shell, printed with black ink, contains the following inactive ingredients: gelatin, titanium dioxide, FD&C blue 1; brilliant blue FCF, yellow iron oxide and black iron oxide.

12 CLINICAL PHARMACOLOGY

12.1 Mechanism of Action

The mechanism by which dimethyl fumarate (DMF) exerts its therapeutic effect in multiple sclerosis is unknown. DMF and the metabolite, monomethyl fumarate (MMF), have been shown to activate the Nuclear factor (erythroid-derived 2)-like 2 (Nrf2) pathway in vitro and in vivo in animals and humans. The Nrf2 pathway is involved in the cellular response to oxidative stress. MMF has been identified as a nicotinic acid receptor agonist in vitro.

12.2 Pharmacodynamics

Potential to prolong the QT interval

In a placebo controlled thorough QT study performed in healthy subjects, there was no evidence that dimethyl fumarate caused QT interval prolongation of clinical significance (i.e., the upper bound of the 90% confidence interval for the largest placebo-adjusted, baseline-corrected QTc was below 10 ms).

12.3 Pharmacokinetics

After oral administration of TECFIDERA, dimethyl fumarate undergoes rapid presystemic hydrolysis by esterases and is converted to its active metabolite, monomethyl fumarate (MMF). Dimethyl fumarate is not quantifiable in plasma following oral administration of TECFIDERA. Therefore all pharmacokinetic analyses related to TECFIDERA were performed with plasma MMF concentrations. Pharmacokinetic data were obtained in subjects with multiple sclerosis and healthy volunteers.

Absorption

The median Tmax of MMF is 2-2.5 hours. The peak plasma concentration (Cmax) and overall exposure (AUC) increased approximately dose proportionally in the dose range studied (120 mg to 360 mg). Following administration of TECFIDERA 240 mg twice a day with food, the mean Cmax of MMF was 1.87 mg/L and AUC was 8.21 mg.hr/L in MS patients.

A high-fat, high-calorie meal did not affect the AUC of MMF but decreased its Cmax by 40%. The Tmax was delayed from 2.0 hours to 5.5 hours. In this study, the incidence of flushing was reduced by approximately 25% in the fed state.

Distribution

The apparent volume of distribution of MMF varies between 53 and 73 L in healthy subjects. Human plasma protein binding of MMF is 27-45% and independent of concentration.

Metabolism

In humans, dimethyl fumarate is extensively metabolized by esterases, which are ubiquitous in the gastrointestinal tract, blood, and tissues, before it reaches the systemic circulation. Further metabolism of MMF occurs through the tricarboxylic acid (TCA) cycle, with no involvement of the cytochrome P450 (CYP) system. MMF, fumaric and citric acid, and glucose are the major metabolites in plasma.

Elimination

Exhalation of CO2 is the primary route of elimination, accounting for approximately 60% of the TECFIDERA dose. Renal and fecal elimination are minor routes of elimination, accounting for 16% and 1% of the dose respectively. Trace amounts of unchanged MMF were present in urine.

The terminal half-life of MMF is approximately 1 hour and no circulating MMF is present at 24 hours in the majority of individuals. Accumulation of MMF does not occur with multiple doses of TECFIDERA.

Specific Populations

Body weight, gender, and age do not require dosage adjustment.

No studies have been conducted in subjects with hepatic or renal impairment. However, neither condition would be expected to affect exposure to MMF and therefore no dosage adjustment is necessary.

Drug Interaction Studies

No potential drug interactions with dimethyl fumarate or MMF were identified in in vitro CYP inhibition and induction studies, or in P-glycoprotein studies. Single doses of interferon beta-1a or glatiramer acetate did not alter the pharmacokinetics of MMF. Aspirin, when administered approximately 30 minutes before TECFIDERA, did not alter the pharmacokinetics of MMF.

Oral Contraceptives

The coadministration of dimethyl fumarate with a combined oral contraceptive (norelgestromin and ethinyl estradiol) did not elicit any relevant effects in oral contraceptives exposure. No interaction studies have been performed with oral contraceptives containing other progestogens.

Vaccines

A randomized, open-label study examined the concomitant use of TECFIDERA and several non-live vaccines in adults 27-55 years of age with relapsing forms of MS (38 subjects undergoing treatment with TECFIDERA at the time of vaccination and 33 subjects undergoing treatment with non-pegylated interferon at the time of vaccination). Concomitant exposure to TECFIDERA did not attenuate antibody responses to tetanus toxoid-containing vaccine, pneumococcal polysaccharide, and meningococcal vaccines relative to antibody responses in interferon-treated patients. The impact of these findings on vaccine effectiveness in this patient population is unknown. The safety and effectiveness of live or live-attenuated vaccines administered concomitantly with TECFIDERA have not been assessed.

13 NONCLINICAL TOXICOLOGY

13.1 Carcinogenesis, Mutagenesis, Impairment of Fertility

Carcinogenesis

Carcinogenicity studies of dimethyl fumarate (DMF) were conducted in mice and rats. In mice, oral administration of DMF (25, 75, 200, and 400 mg/kg/day) for up to two years resulted in an increase in nonglandular stomach (forestomach) and kidney tumors: squamous cell carcinomas and papillomas of the forestomach in males and females at 200 and 400 mg/kg/day; leiomyosarcomas of the forestomach at 400 mg/kg/day in males and females; renal tubular adenomas and carcinomas at 200 and 400 mg/kg/day in males; and renal tubule adenomas at 400 mg/kg/day in females. Plasma MMF exposure (AUC) at the highest dose not associated with tumors in mice (75 mg/kg/day) was similar to that in humans at the recommended human dose (RHD) of 480 mg/day.

In rats, oral administration of DMF (25, 50, 100, and 150 mg/kg/day) for up to two years resulted in increases in squamous cell carcinomas and papillomas of the forestomach at all doses tested in males and females, and in testicular interstitial (Leydig) cell adenomas at 100 and 150 mg/kg/day. Plasma MMF AUC at the lowest dose tested was lower than that in humans at the RHD.

Mutagenesis

Dimethyl fumarate (DMF) and monomethyl fumarate (MMF) were not mutagenic in the in vitro bacterial reverse mutation (Ames) assay. DMF and MMF were clastogenic in the in vitro chromosomal aberration assay in human peripheral blood lymphocytes in the absence of metabolic activation. DMF was not clastogenic in the in vivo micronucleus assay in the rat.

Impairment of Fertility

In male rats, oral administration of DMF (75, 250, and 375 mg/kg/day) prior to and throughout the mating period had no effect on fertility; however, increases in non-motile sperm were observed at the mid and high doses. The no-effect dose for adverse effects on sperm is similar to the recommended human dose (RHD) of 480 mg/day on a body surface area (mg/m^2) basis.

In female rats, oral administration of DMF (20, 100, and 250 mg/kg/day) prior to and during mating and continuing to gestation day 7 caused disruption of the estrous cycle and increases in embryolethality at the highest dose tested. The highest dose not associated with adverse effects (100 mg/kg/day) is twice the RHD on a mg/m^2 basis.

Testicular toxicity (germinal epithelial degeneration, atrophy, hypospermia, and/or hyperplasia) was observed at clinically relevant doses in mice, rats, and dogs in subchronic and chronic oral toxicity studies of DMF, and in a chronic oral toxicity study evaluating a combination of four fumaric acid esters (including DMF) in rats.

13.2 Animal Toxicology and/or Pharmacology

Kidney toxicity was observed after repeated oral administration of dimethyl fumarate (DMF) in mice, rats, dogs, and monkeys. Renal tubule epithelia regeneration, suggestive of tubule epithelial injury, was observed in all species. Renal tubular hyperplasia was observed in rats with dosing for up to two years. Cortical atrophy and interstitial fibrosis were observed in dogs and monkeys at doses above 5 mg/kg/day. In monkeys, the highest dose tested (75 mg/kg/day) was associated with single cell necrosis and multifocal and diffuse interstitial fibrosis, indicating irreversible loss of renal tissue and function. In dogs and monkeys, the 5 mg/kg/day dose was associated with plasma MMF exposures less than or similar to that in humans at the recommended human dose (RHD).

A dose-related increase in incidence and severity of retinal degeneration was observed in mice following oral administration of DMF for up to two years at doses above 75 mg/kg/day, a dose associated with plasma MMF exposure (AUC) similar to that in humans at the RHD.

14 CLINICAL STUDIES

The efficacy and safety of TECFIDERA were demonstrated in two studies (Studies 1 and 2) that evaluated TECFIDERA taken either twice or three times a day in patients with relapsing-remitting multiple sclerosis (RRMS). The starting dose for TECFIDERA was 120 mg twice or three times a day for the first 7 days, followed by an increase to 240 mg twice or three times a day. Both studies included patients who had experienced at least 1 relapse over the year preceding the trial or had a brain Magnetic Resonance Imaging (MRI) scan demonstrating at least one gadolinium-enhancing (Gd+) lesion within 6 weeks of randomization. The Expanded Disability Status Scale (EDSS) was also assessed and patients could have scores ranging from 0 to 5. Neurological evaluations were performed at baseline, every 3 months, and at the time of suspected relapse. MRI evaluations were performed at baseline, month 6, and year 1 and 2 in a subset of patients (44% in Study 1 and 48% in Study 2).

Study 1: Placebo-Controlled Trial in RRMS

Study 1 was a 2-year randomized, double-blind, placebo-controlled study in 1234 patients with RRMS. The primary endpoint was the proportion of patients relapsed at 2 years. Additional endpoints at 2 years included the number of new or newly enlarging T2 hyperintense lesions, number of new T1 hypointense lesions, number of Gd+ lesions, annualized relapse rate (ARR), and time to confirmed disability progression. Confirmed disability progression was defined as at least a 1 point increase from baseline EDSS (1.5 point increase for patients with baseline EDSS of 0) sustained for 12 weeks.

Patients were randomized to receive TECFIDERA 240 mg twice a day (n=410), TECFIDERA 240 mg three times a day (n=416), or placebo (n=408) for up to 2 years. The median age was 39 years, median time since diagnosis was 4 years, and median EDSS score at baseline was 2. The median time on study drug for all treatment arms was 96 weeks. The percentages of patients who completed 96 weeks on study drug per treatment group were 69% for patients assigned to TECFIDERA 240 mg twice a day, 69% for patients assigned to TECFIDERA 240 mg three times a day and 65% for patients assigned to placebo groups.

TECFIDERA had a statistically significant effect on all of the endpoints described above and the 240 mg three times daily dose showed no additional benefit over the TECFIDERA 240 mg twice daily dose. The results for this study (240 mg twice a day vs. placebo) are shown in Table 2 and Figure 1.

Table 2: Clinical and MRI Results of Study 1
 | TECFIDERA 240 mg BID | Placebo | P-value
Clinical Endpoints | N=410 | N=408
Proportion relapsing (primary endpoint) Relative risk reduction | 27% 49% | 46% | <0.0001
Annualized relapse rate | 0.172 | 0.364 | <0.0001
Relative reduction | 53%
Proportion with disability progression | 16% | 27% | 0.0050
Relative risk reduction | 38%
MRI Endpoints | N=152 | N=165
Mean number of new or newly enlarging | 2.6 | 17 | <0.0001
T2 lesions over 2 years
Percentage of subjects with no new or newly enlarging lesions | 45% | 27%
Number of Gd+ lesions at 2 years | 0.1 (0) | 1.8 (0)
Mean (median)
Percentage of subjects with
0 lesions | 93% | 62%
1 lesion | 5% | 10%
2 lesions | <1% | 8%
3 to 4 lesions | 0 | 9%
5 or more lesions | <1% | 11%
Relative odds reduction | 90% |  | <0.0001
(percentage)
Mean number of new T1 hypointense | 1.5 | 5.6 | <0.0001
lesions over 2 years

Figure 1: Time to 12-Week Confirmed Progression of Disability (Study 1)

Study 2: Placebo-Controlled Trial in RRMS

Study 2 was a 2-year multicenter, randomized, double-blind, placebo-controlled study that also included an open-label comparator arm in patients with RRMS. The primary endpoint was the annualized relapse rate at 2 years. Additional endpoints at 2 years included the number of new or newly enlarging T2 hyperintense lesions, number of T1 hypointense lesions, number of Gd+ lesions, proportion of patients relapsed, and time to confirmed disability progression as defined in Study 1.

Patients were randomized to receive TECFIDERA 240 mg twice a day (n=359), TECFIDERA 240 mg three times a day (n=345), an open-label comparator (n=350), or placebo (n=363) for up to 2 years. The median age was 37 years, median time since diagnosis was 3 years, and median EDSS score at baseline was 2.5. The median time on study drug for all treatment arms was 96 weeks. The percentages of patients who completed 96 weeks on study drug per treatment group were 70% for patients assigned to TECFIDERA 240 mg twice a day, 72% for patients assigned to TECFIDERA 240 mg three times a day and 64% for patients assigned to placebo groups.

TECFIDERA had a statistically significant effect on the relapse and MRI endpoints described above. There was no statistically significant effect on disability progression. The TECFIDERA 240 mg three times daily dose resulted in no additional benefit over the TECFIDERA 240 mg twice daily dose. The results for this study (240 mg twice a day vs. placebo) are shown in Table 3.

Table 3: Clinical and MRI Results of Study 2
 | TECFIDERA 240 mg BID | Placebo | P-value
Clinical Endpoints | N=359 | N=363
Annualized relapse rate | 0.224 | 0.401 | <0.0001
Relative reduction | 44%
Proportion relapsing | 29% | 41% | 0.0020
Relative risk reduction | 34%
Proportion with disability progression | 13% | 17% | 0.25
Relative risk reduction | 21%
MRI Endpoints | N=147 | N=144
Mean number of new or newly enlarging | 5.1 | 17.4 | <0.0001
T2 lesions over 2 years
Percentage of subjects with no new or | 27% | 12%
newly enlarging lesions
Number of Gd+ lesions at 2 years
Mean (median) | 0.5 (0.0) | 2.0 (0.0)
Percentage of subjects with
0 lesions | 80% | 61%
1 lesion | 11% | 17%
2 lesions | 3% | 6%
3 to 4 lesions | 3% | 2%
5 or more lesions | 3% | 14%
Relative odds reduction | 74% |  | <0.0001
(percentage)
Mean number of new T1 hypointense | 3.0 | 7.0 | <0.0001
lesions over 2 years

16 HOW SUPPLIED/STORAGE AND HANDLING

TECFIDERA is available as hard gelatin delayed-release capsules in two strengths containing either 120 mg or 240 mg of dimethyl fumarate. The green and white 120 mg capsules are printed with “BG-12 120 mg” in black ink. The green 240 mg capsules are printed with “BG-12 240 mg” in black ink. TECFIDERA is available as follows:

30-day Starter Pack, (NDC 64406-007-03):

7-day bottle 120 mg capsules, quantity 14
23-day bottle 240 mg capsules, quantity 46

120 mg capsules:

7-day bottle of 14 capsules (NDC 64406-005-01)

240 mg capsules:

30-day bottle of 60 capsules (NDC 64406-006-02)

Store at 15°C to 30°C (59 to 86°F). Protect the capsules from light. Store in original container.

17 PATIENT COUNSELING INFORMATION

Advise the patient to read the FDA-approved patient labeling (Patient Information).

Dosage

Inform patients that they will be provided two strengths of TECFIDERA when starting treatment: 120 mg capsules for the 7 day starter dose and 240 mg capsules for the maintenance dose, both to be taken twice daily. Inform patients to swallow TECFIDERA capsules whole and intact. Inform patients to not crush, chew, or sprinkle capsule contents on food. Inform patients that TECFIDERA can be taken with or without food [see Dosage and Administration (2.1)].

Anaphylaxis and Angioedema

Advise patients to discontinue TECFIDERA and seek medical care if they develop signs and symptoms of anaphylaxis or angioedema [see Warnings and Precautions (5.1)].

Progressive Multifocal Leukoencephalopathy

Inform patients that progressive multifocal leukoencephalopathy (PML) has occurred in patients who received TECFIDERA. Inform the patient that PML is characterized by a progression of deficits and usually leads to death or severe disability over weeks or months. Instruct the patient of the importance of contacting their doctor if they develop any symptoms suggestive of PML. Inform the patient that typical symptoms associated with PML are diverse, progress over days to weeks, and include progressive weakness on one side of the body or clumsiness of limbs, disturbance of vision, and changes in thinking, memory, and orientation leading to confusion and personality changes [see Warnings and Precautions (5.2)].

Herpes Zoster and Other Serious Opportunistic Infections

Inform patients that herpes zoster and other serious opportunistic infections have occurred in patients who received TECFIDERA. Instruct the patient of the importance of contacting their doctor if they develop any signs or symptoms associated with herpes zoster or other serious opportunistic infections [see Warnings and Precautions (5.3)].

Lymphocyte Counts

Inform patients that TECFIDERA may decrease lymphocyte counts. A blood test should be obtained before they start therapy. Blood tests are also recommended after 6 months of treatment, every 6 to 12 months thereafter, and as clinically indicated [see Warnings and Precautions (5.3), Adverse Reactions (6.1)].

Liver Injury

Inform patients that TECFIDERA may cause liver injury. Instruct patients treated with TECFIDERA to report promptly any symptoms that may indicate liver injury, including fatigue, anorexia, right upper abdominal discomfort, dark urine, or jaundice. A blood test should be obtained before patients start therapy and during treatment, as clinically indicated [see Warnings and Precautions (5.4)].

Flushing

Inform patients that flushing is one of the most common reactions, especially at the initiation of therapy, and may decrease over time. Advise patients to contact their healthcare provider if they experience persistent and/or severe flushing. Advise patients experiencing flushing that taking TECFIDERA with food or taking a non-enteric coated aspirin prior to taking TECFIDERA may help [see Adverse Reactions (6.1)].

Gastrointestinal (GI) Events

Inform patients that GI events (abdominal pain, diarrhea, and nausea) are some of the most common adverse reactions, especially at the initiation of therapy, and may decrease over time. Some patients may experience more severe GI events. Advise patients to immediately contact their healthcare provider and discontinue TECFIDERA if they experience gastrointestinal bleeding (e.g., rectal bleeding, bloody diarrhea, hematemesis) or other serious gastrointestinal adverse events (e.g., severe abdominal pain, severe vomiting and/or diarrhea) [see Warnings and Precautions (5.7)].

PPI-41347-18

Manufactured for:
Biogen Inc.
Cambridge, MA 02142

TECFIDERA is a registered trademark of Biogen.

© Biogen 2013 - 2024

Patient Information
TECFIDERA® (tek" fi de' rah)
(dimethyl fumarate) delayed-release capsules

What is TECFIDERA?

- TECFIDERA is a prescription medicine used to treat relapsing forms of multiple sclerosis (MS), to include clinically isolated syndrome, relapsing-remitting disease, and active secondary progressive disease, in adults.
- It is not known if TECFIDERA is safe and effective in children under 18 years of age.

Who should not take TECFIDERA?

- Do not use TECFIDERA if you have had an allergic reaction (such as welts, hives, swelling of the face, lips, mouth or tongue, or difficulty breathing) to TECFIDERA or any of its ingredients. See below for a complete list of ingredients.

Before taking and while you take TECFIDERA, tell your doctor if you have or have had:

- low white blood cell counts or an infection
- any other medical conditions

Tell your doctor if you are:

- pregnant or plan to become pregnant. It is not known if TECFIDERA will harm your unborn baby. You and your doctor will have to decide if you should take TECFIDERA while you are pregnant or if you plan to become pregnant.
- breastfeeding or plan to breastfeed. It is not known if TECFIDERA passes into your breast milk. You and your doctor should decide if you will take TECFIDERA or breastfeed.taking prescription or over-the-counter medicines, vitamins, or herbal supplements

How should I take TECFIDERA?

- Take TECFIDERA exactly as your doctor tells you to take it
- The recommended starting dose is one 120 mg capsule taken by mouth 2 times a day for 7 days
- The recommended dose after 7 days is one 240 mg capsule taken by mouth 2 times a day
- TECFIDERA can be taken with or without food
- Swallow TECFIDERA whole. Do not crush, chew, or sprinkle capsule contents on food.
- Protect TECFIDERA from light. You can do this by storing the capsules in their original container.
- If you take too much TECFIDERA, call your doctor or go to the nearest hospital emergency room right away.

What are the possible side effects of TECFIDERA?
TECFIDERA may cause serious side effects including:

- allergic reaction (such as welts, hives, swelling of the face, lips, mouth or tongue, or difficulty breathing)
- PML a rare brain infection that usually leads to death or severe disability
- decreases in your white blood cell count Your doctor should do a blood test before you start treatment with TECFIDERA and while on therapy.
- liver problems. Your doctor should do blood tests to check your liver function before you start taking TECFIDERA and during treatment if needed. Tell your doctor right away if you get any of these symptoms of a liver problem during treatment.
  - severe tiredness
  - loss of appetite
  - pain on the right side of your stomach
  - have dark or brown (tea color) urine
  - yellowing of your skin or the white part of your eyes
- herpes zoster infections (shingles), including central nervous system infections
- other serious infections
- serious gastrointestinal problems, including bleeding, ulcers, blockage, and tears (perforation) of the stomach or intestines. Tell your healthcare provider right away if you have any of these symptoms during treatment:
  - Stomach-area pain that does not go away
  - Bright red or black stools (that look like tar)
  - Severe vomiting
  - Severe diarrhea
  - Coughing up blood or blood clots
  - Vomiting blood or your vomit looks like "coffee grounds"

The most common side effects of TECFIDERA include:

- flushing, redness, itching, or rash
- nausea, vomiting, diarrhea, stomach pain, or indigestion. These events can be serious in some patients (see "TECFIDERA may cause serious side effects including," above).
- Flushing and stomach problems are the most common reactions, especially at the start of therapy, and may decrease over time. Taking TECFIDERA with food may help reduce flushing. Call your doctor if you have any of these symptoms and they bother you or do not go away. Ask your doctor if taking aspirin before taking TECFIDERA may reduce flushing.

These are not all the possible side effects of TECFIDERA. Call your doctor for medical advice about side effects. You may report side effects to FDA at 1-800-FDA-1088. For more information go to dailymed.nlm.nih.gov.

General Information about the safe and effective use of TECFIDERA

- Medicines are sometimes prescribed for purposes other than those listed in this Patient Information. Do not use TECFIDERA for a condition for which it was not prescribed. Do not give TECFIDERA to other people, even if they have the same symptoms that you have. It may harm them.
- If you would like more information, talk to your doctor or pharmacist. You can ask your doctor or pharmacist for information about TECFIDERA that is written for healthcare professionals.

What are the ingredients in TECFIDERA?
Active ingredient: dimethyl fumarate
Inactive ingredients: microcrystalline cellulose, silicified microcrystalline cellulose, croscarmellose sodium, talc, silica colloidal silicon dioxide, magnesium stearate, triethyl citrate, methacrylic acid copolymer - Type A, methacrylic acid copolymer dispersion, simethicone (30% emulsion), sodium lauryl sulphate, and polysorbate 80. Capsule Shell: gelatin, titanium dioxide, FD&C blue 1; brilliant blue FCF, yellow iron oxide and black iron oxide.
Manufactured for: Biogen Inc., Cambridge, MA 02142, www.TECFIDERA.com or call 1-800-456-2255

This Patient Information has been approved by the U.S. Food and Drug Administration. Revised: 03/2024

PPI-41347-3

Principal Display Panel - 240 mg Capsules: Box Label

NDC 64406-006-02

60 capsules

Tecfidera®

(dimethyl fumarate)

delayed-release capsules

240 mg

Dispense in original Package.

Swallow capsule whole.

Rx only

Principal Display Panel - 120 mg Capsules: Box Label

NDC 64406-005-01

14 capsules

Tecfidera®

(dimethyl fumarate)

delayed-release capsules

120 mg

Dispense in original Package.

Swallow capsule whole.

Rx only

Principal Display Panel - 120 mg Capsules: No Charge Box Label

NDC 64406-005-08

14 capsules

Tecfidera®

(dimethyl fumarate)

delayed-release capsules

120 mg

Dispense in original Package.

Swallow capsule whole.

Rx only

Principal Display Panel - 120 mg Capsules: Sample Box Label

NDC 64406-005-10

14 capsules

Tecfidera®

(dimethyl fumarate)

delayed-release capsules

120 mg

Dispense in original Package.

Swallow capsule whole.

Rx only

Principal Display Panel - Starter Pack: Box Label

NDC 64406-007-03

30-Day Starter Pack

Tecfidera®

(dimethyl fumarate)

delayed-release capsules

Package Contents:

120 mg Starter Dose

One bottle containing 14
capsules of 120 mg each

240 mg Regular Dose

One bottle containing 46
capsules of 240 mg each

Dispense in Original Package.

See back panel for dosage and administration
instructions for use.